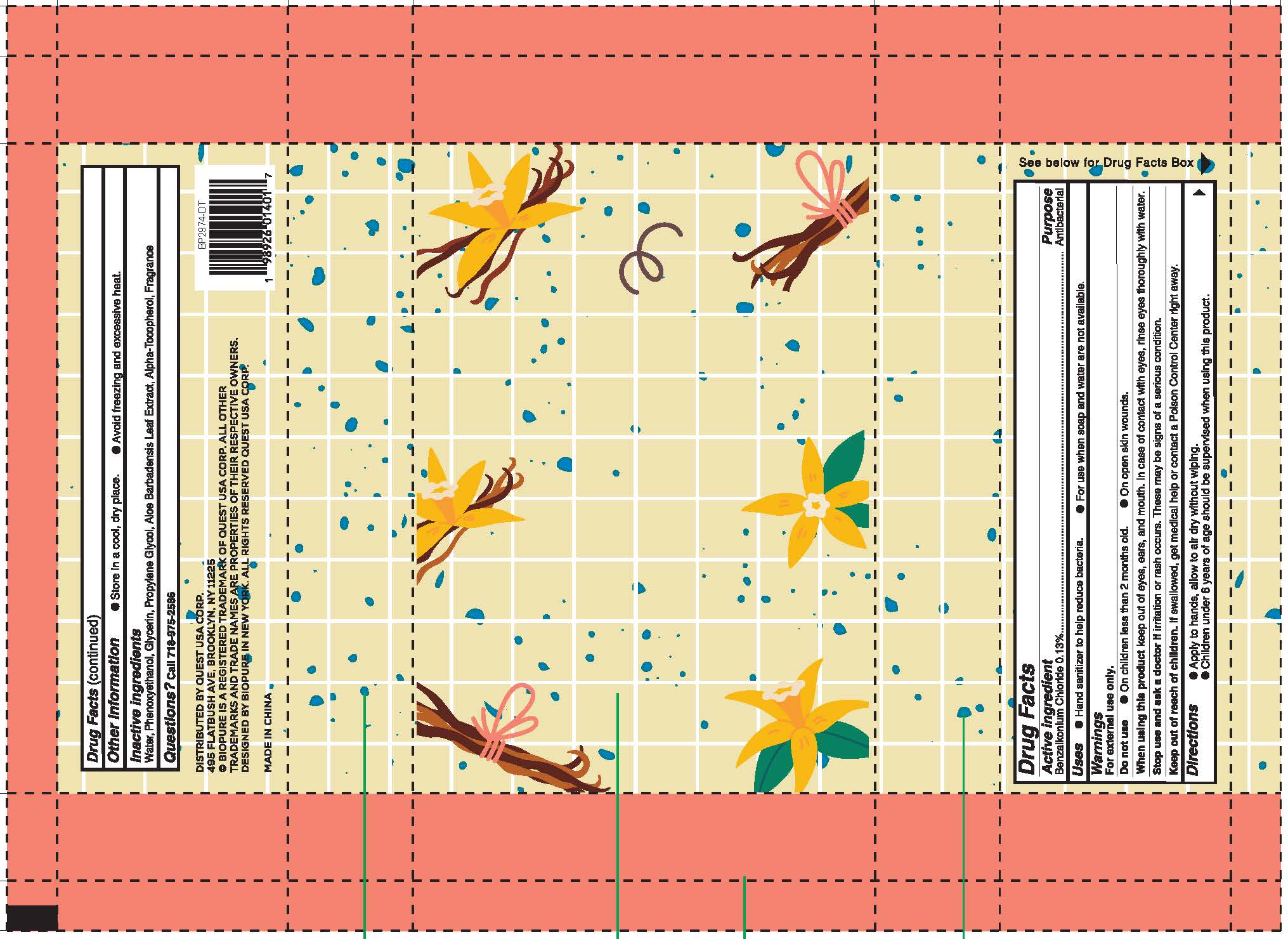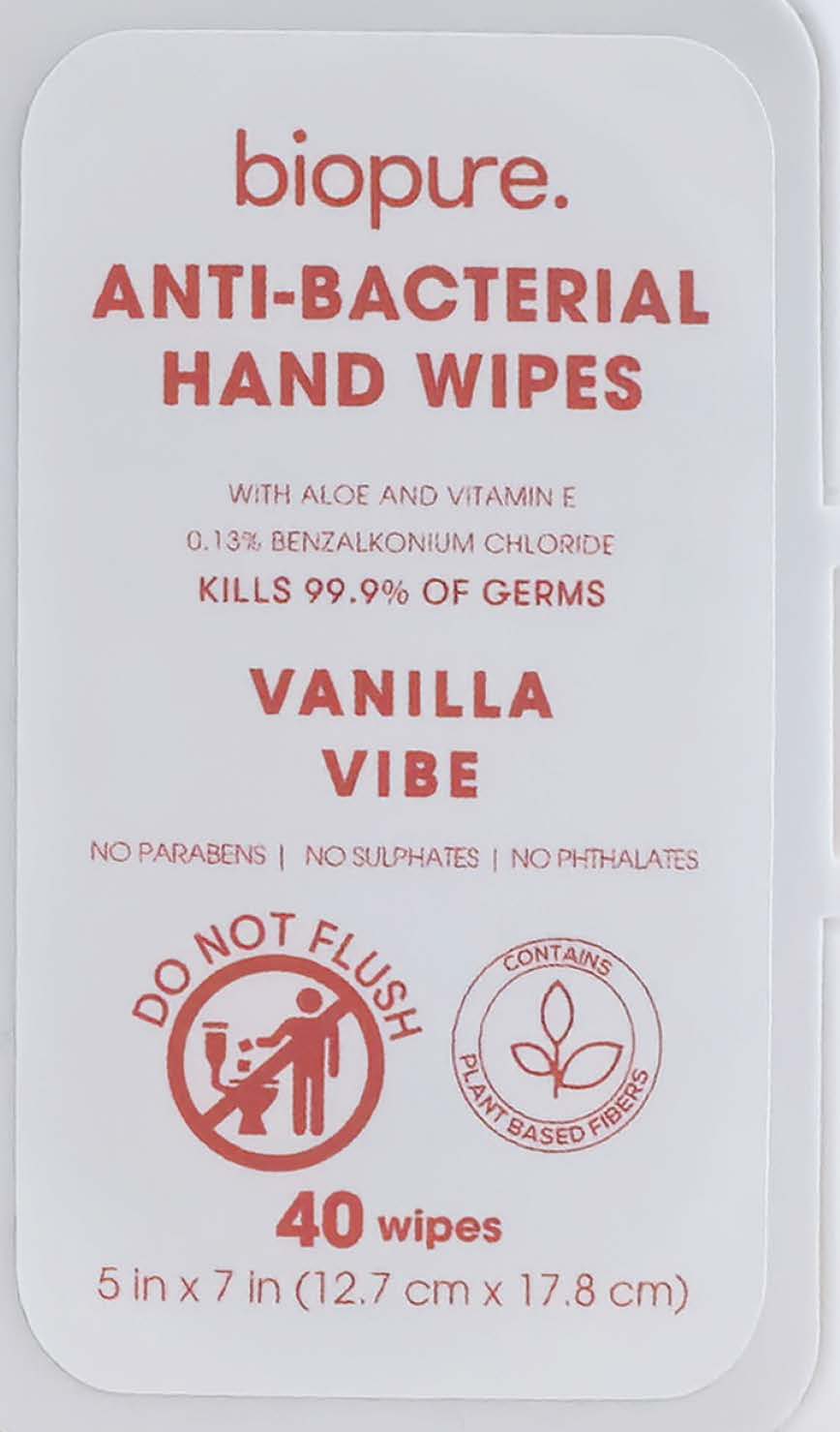 DRUG LABEL: Antibacterial Hand Wipe
NDC: 75543-308 | Form: CLOTH
Manufacturer: Fujian Yifa Healthcare Products Co., Ltd.
Category: otc | Type: HUMAN OTC DRUG LABEL
Date: 20260126

ACTIVE INGREDIENTS: BENZALKONIUM CHLORIDE 0.2 g/40 1
INACTIVE INGREDIENTS: PROPYLENE GLYCOL; ALOE BARBADENSIS LEAF; PHENOXYETHANOL; WATER; GLYCERIN; ALPHA-TOCOPHEROL

BIOPURE Anti-Bacterial Hand Wipes-Vanilla Vibe

Active Ingredient

Benzalkonium Chloride 0.13%

Purpose

Antibacterial

Use

Hand sanitizer to help reduce bacteria;
For use when soap and water are not available.

Warnings

For external use only

Do not use

In children less than 2 months old;
On open skin wounds.

When Using

keep out of eyes,ears,and mouth.In case of contact with eyes,rinse eyes thoroughly with water.

Stop Use

If irritation or rash occurs.These may be signs of a serious condition.

Ask Doctor

If irritation or rash occurs.These may be signs of a serious condition.

Keep Out Of Reach Of Children

If swallowed, get medical help or contact a Poison Control Center right away.

Directions

1.Apply to hands,allow to air dry without wiping;
2.Children under 6 years of age should be supervised when using this product.

Other information

1.Store in a cool,dry place;2.Avoid freezing and excessive heat.

Inactive ingredients

Aloe Barbadensis Leaf Extract,Alpha-Tocopherol,Fragrance,Glycerin,Phenoexyethanol,Propylene Glycol,Water.

Questions

call 718-975-2586